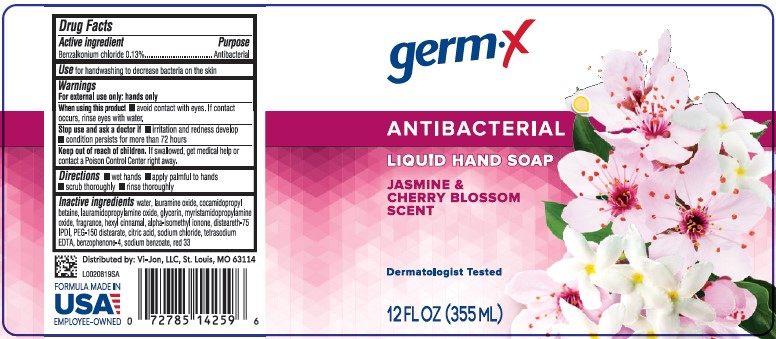 DRUG LABEL: Antibacterial Cherry Blossom
NDC: 83986-913 | Form: SOAP
Manufacturer: UpLift Brands, LLC
Category: otc | Type: HUMAN OTC DRUG LABEL
Date: 20250714

ACTIVE INGREDIENTS: BENZALKONIUM CHLORIDE 1.3 mg/1 mL
INACTIVE INGREDIENTS: WATER; LAURAMINE OXIDE; COCAMIDOPROPYL BETAINE; LAURAMIDOPROPYLAMINE OXIDE; GLYCERIN; MYRISTAMIDOPROPYLAMINE OXIDE; .ALPHA.-HEXYLCINNAMALDEHYDE; ISOMETHYL-.ALPHA.-IONONE; DISTEARETH-75 ISOPHORONE DIISOCYANATE; PEG-150 DISTEARATE; CITRIC ACID MONOHYDRATE; SODIUM CHLORIDE; EDETATE SODIUM; SULISOBENZONE; SODIUM BENZOATE; D&C RED NO. 33

Germ-X D13.000/D13AB
Antibacterial Hand Soap Cherry Blossom

Active Ingredient

Benzalkonium chloride 0.13%

Purpose

Antibacterial

Use

for handwashing to decrease bacteria on the skin

Warnings

For external use only: hands only

When using this product

- avoid contact with eyes. If contact occurs, rinse eyes with water.

Stop use and ask a doctor if

- irritation and redness develop
- condition persists for more than 72 hours

Keep out of reach of children.

If swallowed, get medical help or contact a Poison Control Center right away.

Directions

- wet hands
- apply palmful to hands
- scrub thoroughly
- rinse thoroughly

Inactive Ingredients

water, lauramine oxide, cocamidopropyl betaine, lauramidopropylamine oxide, glycerin, myristamidopropylamine oxide, fragrance, hexyl cinnamal, alpha-isomethyl ionone, disteareth-75 IPDI, PEG-150 distearate, citric acid, sodium chloride, tetrasodium EDTA, benzophenone-4, sodium benzoate, red 33

Adverse reation

Distributed by: Vi-Jon, LLC, St. Louis, MO 63114

FORMULA MADE IN USA

EMPLOYEE-OWNED

Prinsipal Display Panel

germ-x

ANTIBACTERIAL

LIQUID HAND SOAP

JASMINE & CHERRY BLOSSOM SCENT

Dermatologist Tested

12 FL OZ (355 mL)